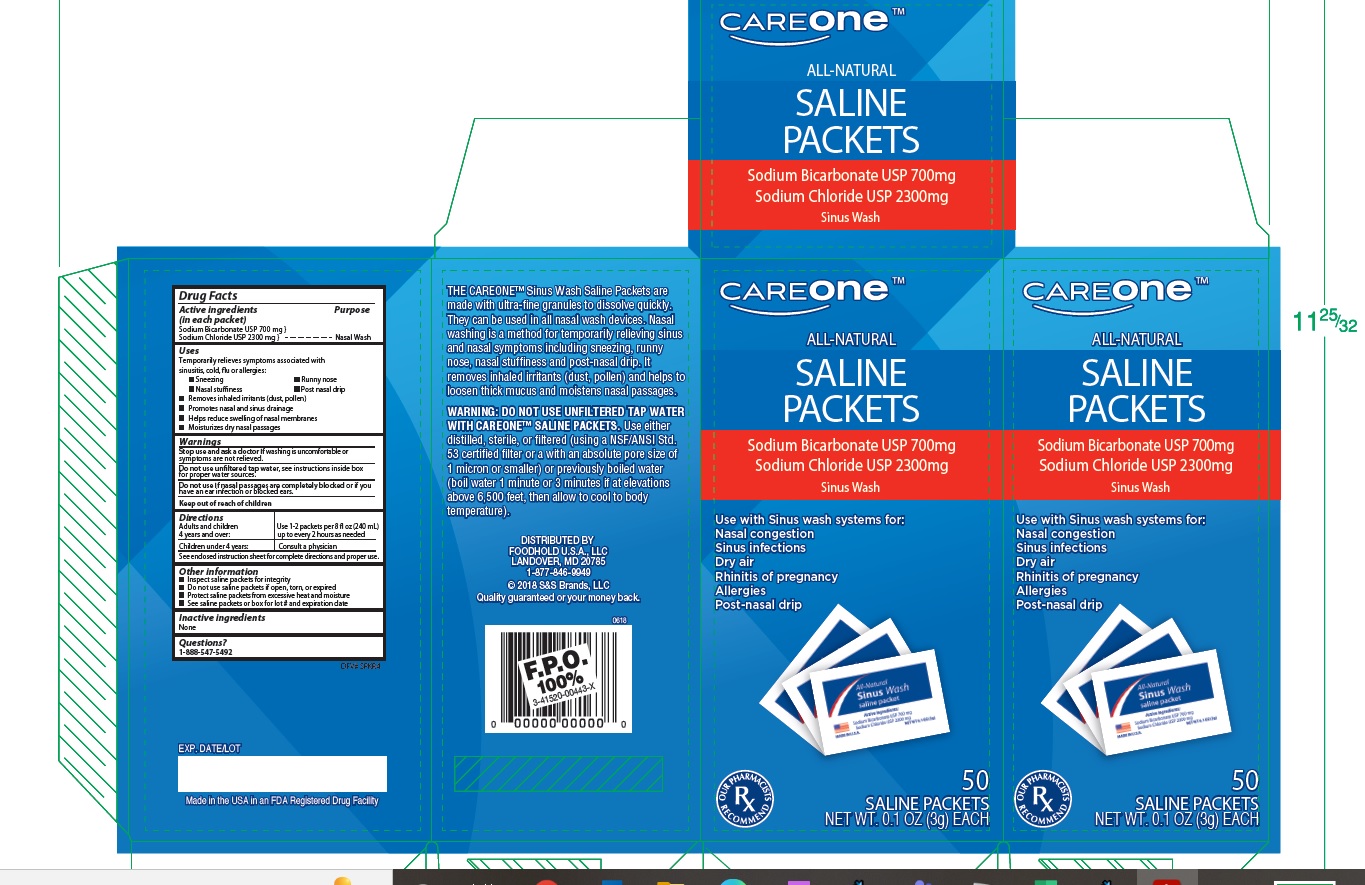 DRUG LABEL: All natural Saline Packets							
NDC: 41520-938 | Form: POWDER, FOR SOLUTION
Manufacturer: FOODHOLD U.S.A.
Category: otc | Type: HUMAN OTC DRUG LABEL
Date: 20251210

ACTIVE INGREDIENTS: SODIUM BICARBONATE 700 mg/3000 mg; SODIUM CHLORIDE 2300 mg/3000 mg
INACTIVE INGREDIENTS: WATER

Care one All natural Saline Refills 50ct

Active ingredients

(in each packet)

Sodium Bicarbonate USP (700 mg)

Sodium Chloride USP (2300 mg)

Purpose

Nasal Wash

Uses

Temporarily relieves symptoms associated with

sinusitis, cold, flu or allergies

-Sneezing

-Nasal stuffiness

-Runny nose

-Post nasal drip

Removes inhaled irritants (dust, pollen)

Removes nasal and sinus drainage

Helps reduce swelling of nasal membranes

Moisturizes dry nasal passages

Keep out of reach of children

Warnings

Stop use and ask a doctor if washing is uncomfortable or symptoms are not relieved.

Do not use unfiltered tap water. see instructions inside box for proper water sources

Do not use if nasal passages are completely blocked or if you have an ear infection or blocked ears

Directions

Adults and children 4 years and over: Use 1-2 packets per 8 fl oz (240 mL) up to every 2 hours as needed.

Children under 4 years: Consult a physician

See enclosed instruction sheet for complete directions and proper use.

Inactive ingredients

None

Other Information

-Inspect saline packets for integrity

-Do not use saline packets if open or torn

-Protect saline packets from excessive heat and moisture

-See saline packets or box for lot # and expiration date

Questions?

1-888-547-5492

OTHER SAFETY INFORMATION

-See instruction sheet for use